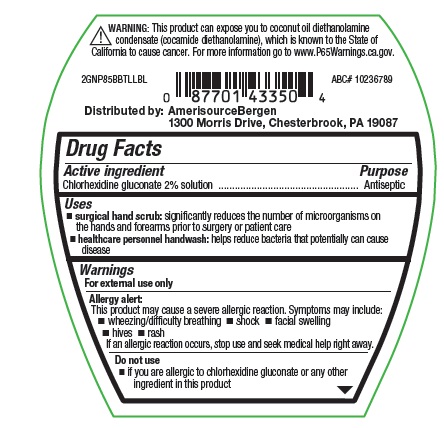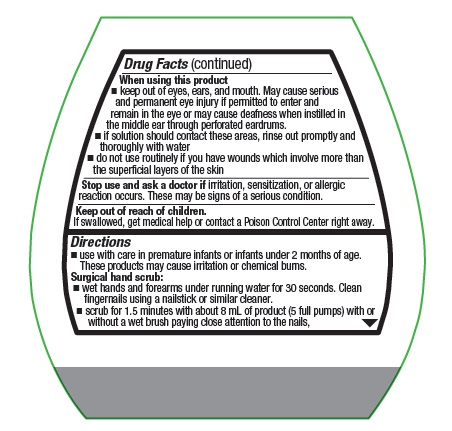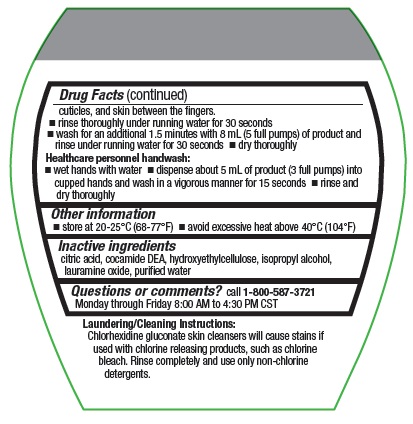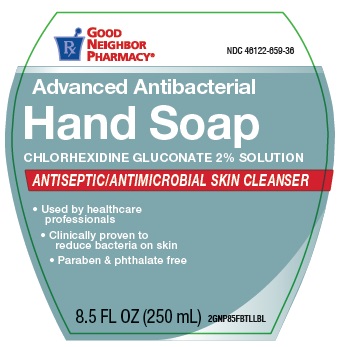 DRUG LABEL: Antiseptic Skin Cleanser
NDC: 46122-659 | Form: SOLUTION
Manufacturer: AmerisourceBergen Drug Corporation
Category: otc | Type: HUMAN OTC DRUG LABEL
Date: 20251212

ACTIVE INGREDIENTS: CHLORHEXIDINE GLUCONATE 2 mg/100 mL
INACTIVE INGREDIENTS: HYDROXYETHYL CELLULOSE (2000 CPS AT 1%); COCO DIETHANOLAMIDE; WATER; CITRIC ACID MONOHYDRATE; LAURAMINE OXIDE

COMP 2% Good Neighbor Pharmacy

Active ingredient

Chlorhexidine gluconate 2% solution

Purpose

Antiseptic

Uses

- surgical hand scrub: significantly reduces the number of microorganisms on the hands and forearms prior to surgery or patient care
- healthcare personnel handwash: helps reduce bacteria that potentially can cause disease

Warnings

For external use only

Allergy alert: This product may cause severe allergic reaction. Symptoms may include:

- wheezing/difficulty breathing
- shock
- facial swelling
- hives
- rash

If an allergic reaction occurs, stop use and seek medical help right away.

Do not use

- if you are allergic to chlorhexidine gluconate or any other ingredient in this product

When using this product

- keep out of eyes, ears, and mouth. May cause serious and permanent eye injury if permitted to enter and remain in the eye or may cause deafness when instilled in the middle ear through perforated eardrums.
- if solution should contact these areas, rinse out promply and thoroughly with water
- do not use routinely if you have wounds which involve more than the superficial layers of the skin

Stop use and ask a doctor if

irritation, sensitization, or allergic reaction occurs. These may be signs of a serious condition.

Keep out of reach of children

If swallowed, get medical help or contact a Poison Control Center right away.

Directions

- use with care in premature infants or infants under 2 months of age. These products may cause irritation or chemical burns.

Surgical hand scrub:

- wet hands and forearms under running water for 30 seconds. Clean fingernails using a nailstick or similar cleaner.
- scrub for 1.5 minutes with about 8 mL of product (5 full pumps) with or without a wet brush paying close attention to the nails, cuticles, and skin between the fingers.
- rinse thoroughly under running water for 30 seconds
- wash for an additional 1.5 minutes with 8 mL (5 full pumps) of product and rinse under running water for 30 seconds
- dry thoroughly

Healthcare personnel handwash:

- wet hands with water
- dispense about 5 mL of product (3 full pumps) into cupped hands and wash in a vigorous manner for 15 seconds
- rinse and dry thoroughly

Other information

- store at 20-25°C (68-77°F)
- avoid excessive heat above 40°C (104°F)

Inactive ingredients

citric acid, cocamide DEA, hydroxyethylcellulose, isopropyl alcohol, lauramine oxide, purified water

Questions or comments?

call 1-800-587-3721 Monday through Friday 8:00 AM to 4:30 PM CST

OTHER SAFETY INFORMATION

Laundering/Cleaning Instructions:

Chlorhexidine gluconate skin cleansers will cause stains if used with chlorine releasing products, such as chlorine bleach. Rinse completely and use only non-chlorine detergents.

RECENT MAJOR CHANGES

Dosage and administration

PACKAGE LABEL

GOOD NEIGHBOR PHARMACY®

NDC 46122-659-36

Advanced Antibacterial Hand Soap

CHLORHEXIDINE GLUCONATE 2% SOLUTION

ANTISEPTIC/ANTIMICROBIAL SKIN CLEANSER

- Used by healthcare professionals
- Clincally proven to reduce bacteria on skin
- Paraben & phthalate free

8.5 FL OZ (250 mL)

2GNP85FBTLLBL